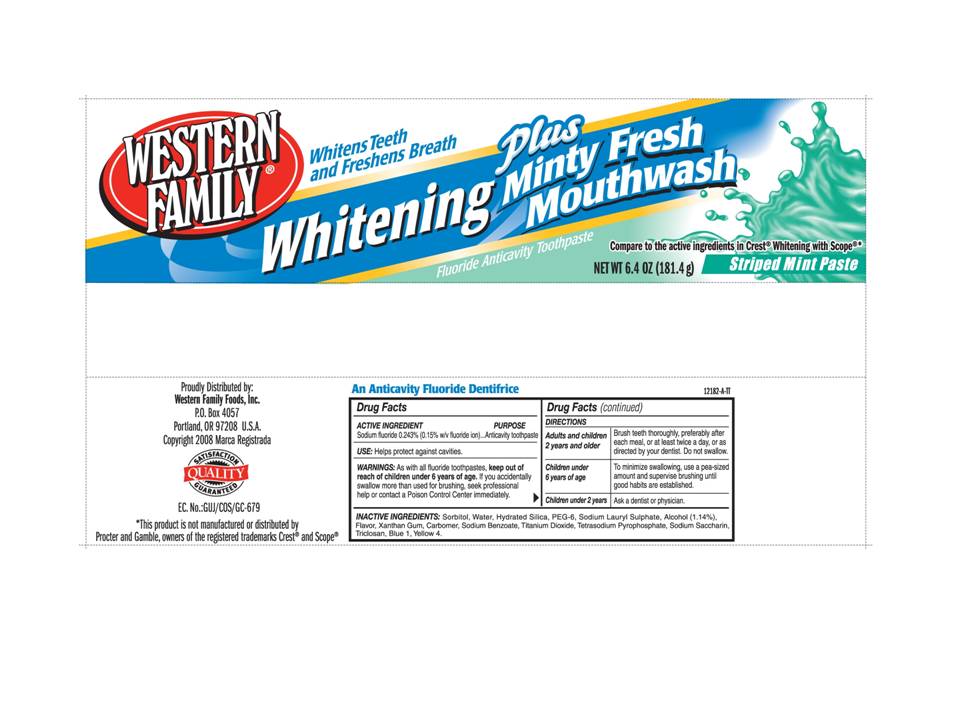 DRUG LABEL: Western Family Whitening Plus Minty Fresh Mouthwash Anticavity
NDC: 55312-182 | Form: PASTE, DENTIFRICE
Manufacturer: Western Family Foods, Inc
Category: otc | Type: HUMAN OTC DRUG LABEL
Date: 20110115

ACTIVE INGREDIENTS: Sodium Fluoride 2.43 mg/1 g
INACTIVE INGREDIENTS: SORBITOL; WATER; HYDRATED SILICA; POLYETHYLENE GLYCOL 300; SODIUM LAURYL SULFATE; ALCOHOL 1.14 mg/1 g; XANTHAN GUM; SODIUM BENZOATE; TITANIUM DIOXIDE; SODIUM PYROPHOSPHATE; SACCHARIN SODIUM; TRICLOSAN

Western Family Whitening Plus Minty Fresh Mouthwash Fluoride Anticavity Toothpaste

Active Ingredient

Sodium Fluoride 0.243% (0.15% w/v fluoride ion)...Anticavity toothpaste

Directions

Adults and children Brush teeth thoroughly, preferably after
2 years and older each meal, or at least twice a day, or as
directed by your dentist. Do not swallow.

Children under To minimize swallowing, use a pea-sized
6 years of age amount and supervise brushing until
good habits are established.

Children under 2 years Ask a dentist or physician.

Inactive Ingredients:

Sorbitol, Water, Hydrated Silica, PEG-6, Sodium Lauryl Sulphate, Alcohol (1.14%), Flavor, Xanthan Gum, Carbomer, Sodium Benzoate, Titanium Dioxide, Tetrasodium Pyrophosphate, Sodium Saccharin, Triclosan, Blue 1, Yellow 4.

WARNINGS

As with all fluoride toothpastes, keep out of reach of children under 6 years of age. If you accidentally swallow more than used for brushing, seek professional help or contact a Poison Control Center immediately.

USE

Helps protect against cavities.